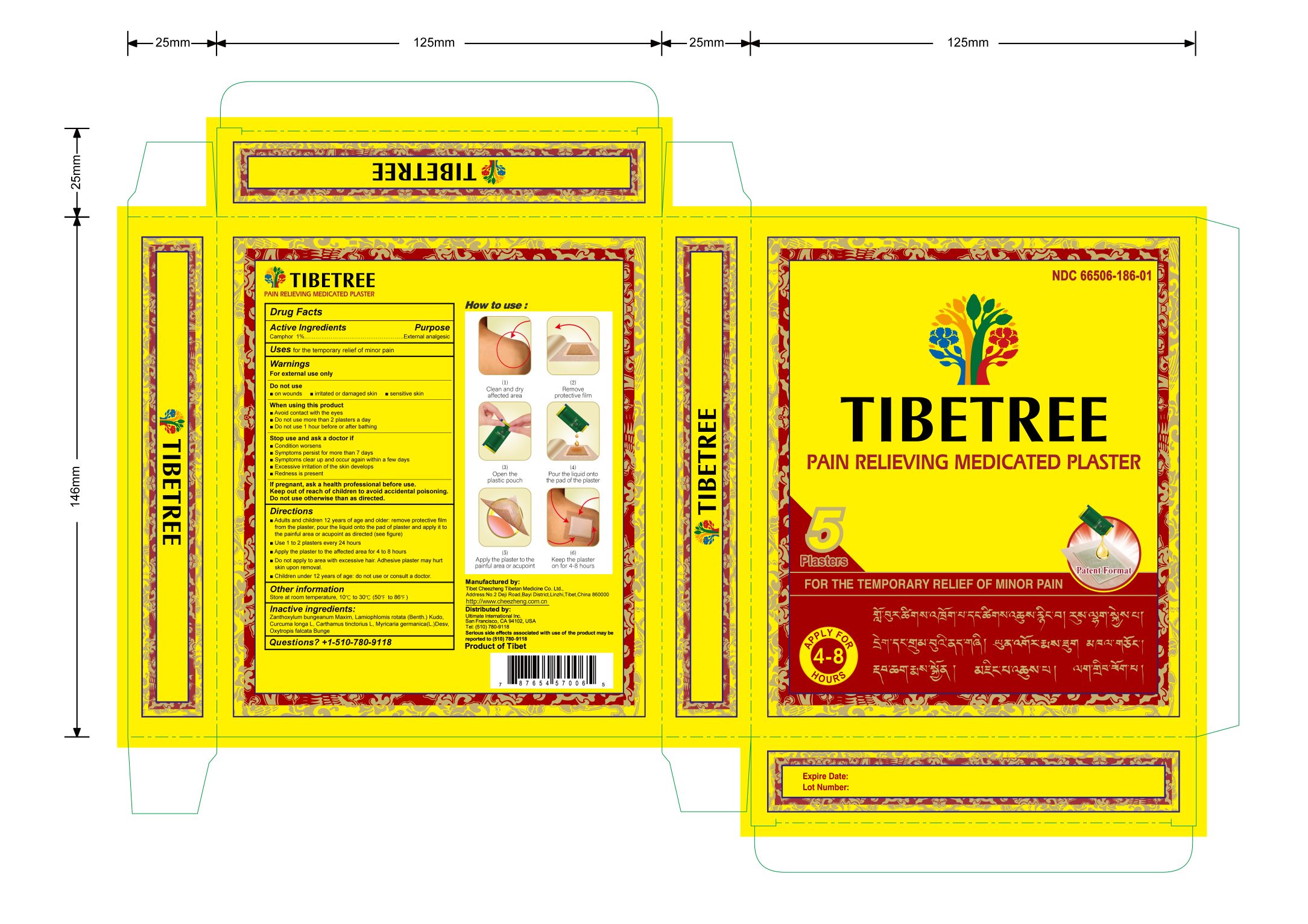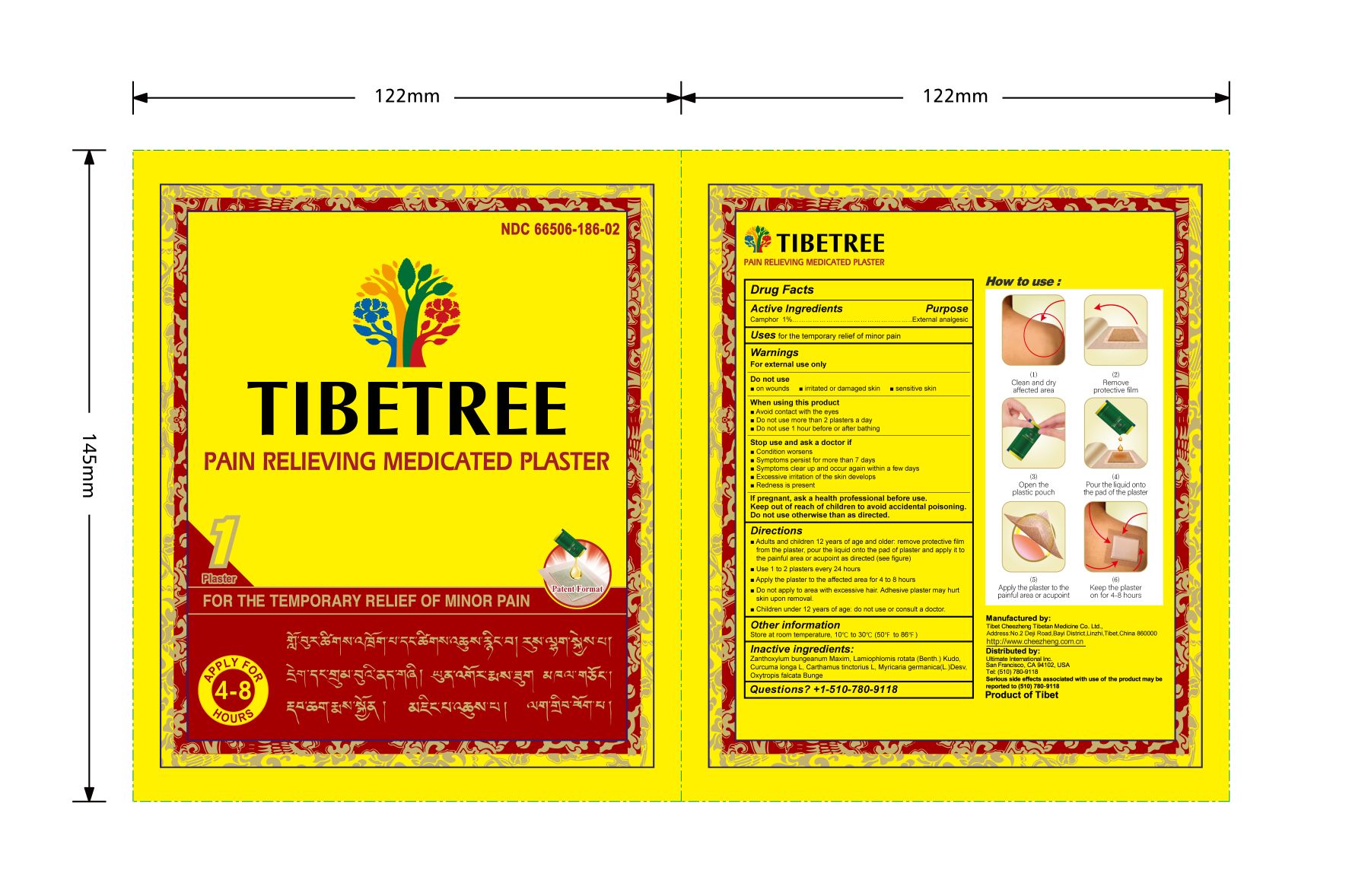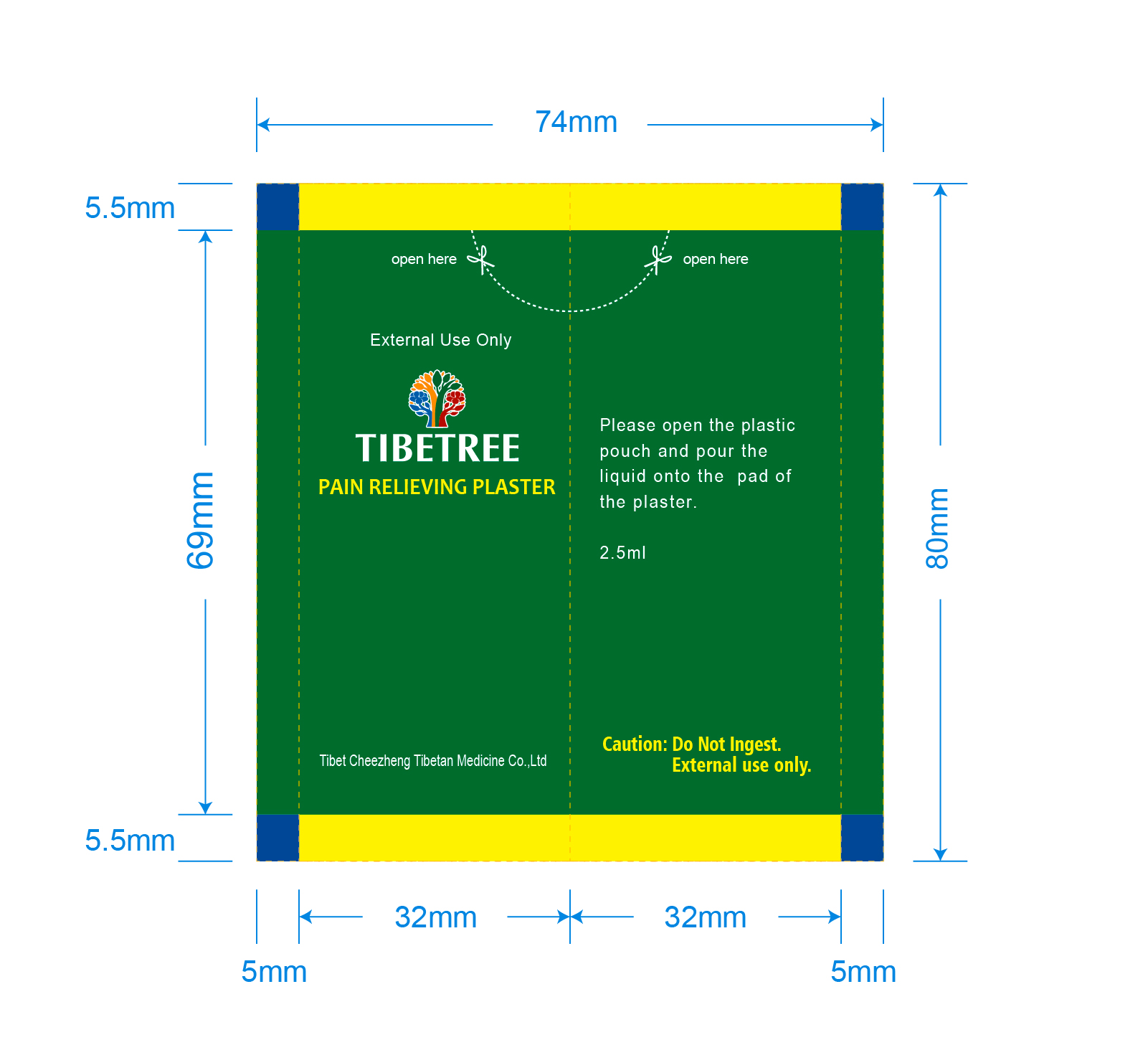 DRUG LABEL: Tibetree Pain Relieveing Medicated Plaster
NDC: 66506-186 | Form: PLASTER
Manufacturer: Tibet Cheezheng Tibetan Medicine Co. Ltd
Category: otc | Type: HUMAN OTC DRUG LABEL
Date: 20250211

ACTIVE INGREDIENTS: CAMPHOR (NATURAL) 1 g/100 g
INACTIVE INGREDIENTS: ZANTHOXYLUM BUNGEANUM FRUIT RIND; CURCUMA LONGA WHOLE; CARTHAMUS TINCTORIUS FLOWER BUD; PHLOMOIDES ROTATA WHOLE; MYRICARIA PANICULATA STEM; OXYTROPIS CHILIOPHYLLA WHOLE

Tibetree Pain Relieveing Plaster

Active ingredients

Camphor 1%.................……….…….External analgesic

Do not use otherwise than as directed

Keep out of reach of children to avoid accidental poisoning

If pregnant

If pregnant, ask a health professional before use

Directions

- Adults and children 12 years of age and older: remove protective film from the plaster, pour the liquid onto the pad of plaster and apply it to the painful area or acupoint as directed (see figure)
- Use 1 to 2 plasters every 24 hours
- Apply the plaster to the affected area for 4 to 8 hours.
- Do not apply to area with excessive hair. Adhesive plaster may hurt skin upon removal.
- Children under 12 years of age: Do not use or consult a doctor.

Other information

store at room temperature, 10° to 30°C(50°F to 86°F)

Inactive ingredients

Zanthoxylum bungeanum, Lamiophlomis rotata, Curcuma longa, Myricaria germanica, Carthamus tinctorius, Oxytropis kansuensis

Questions?

+1-510-780-9118

Purpose

External analgesic

Do not use

- on wounds
- irritated or damaged skin
- sensitive skin

When using this product

- Avoid contact with the eyes
- Do not use more than 2 plasters a day
- Do not use 1 hour before or after bathing

Stop use and ask a doctor if

- Condition worsens
- Symptoms persist for more than 7 days
- Symptoms clear up and occur again within a few days
- Excessive irritation of the skin develops
- Redness is present

Uses

For the temporary relief of minor pain.

Warnings

For external use only

Tibetree PDP

1.jpg

Inner PackageLiquid Package

2.jpg

33.jpg